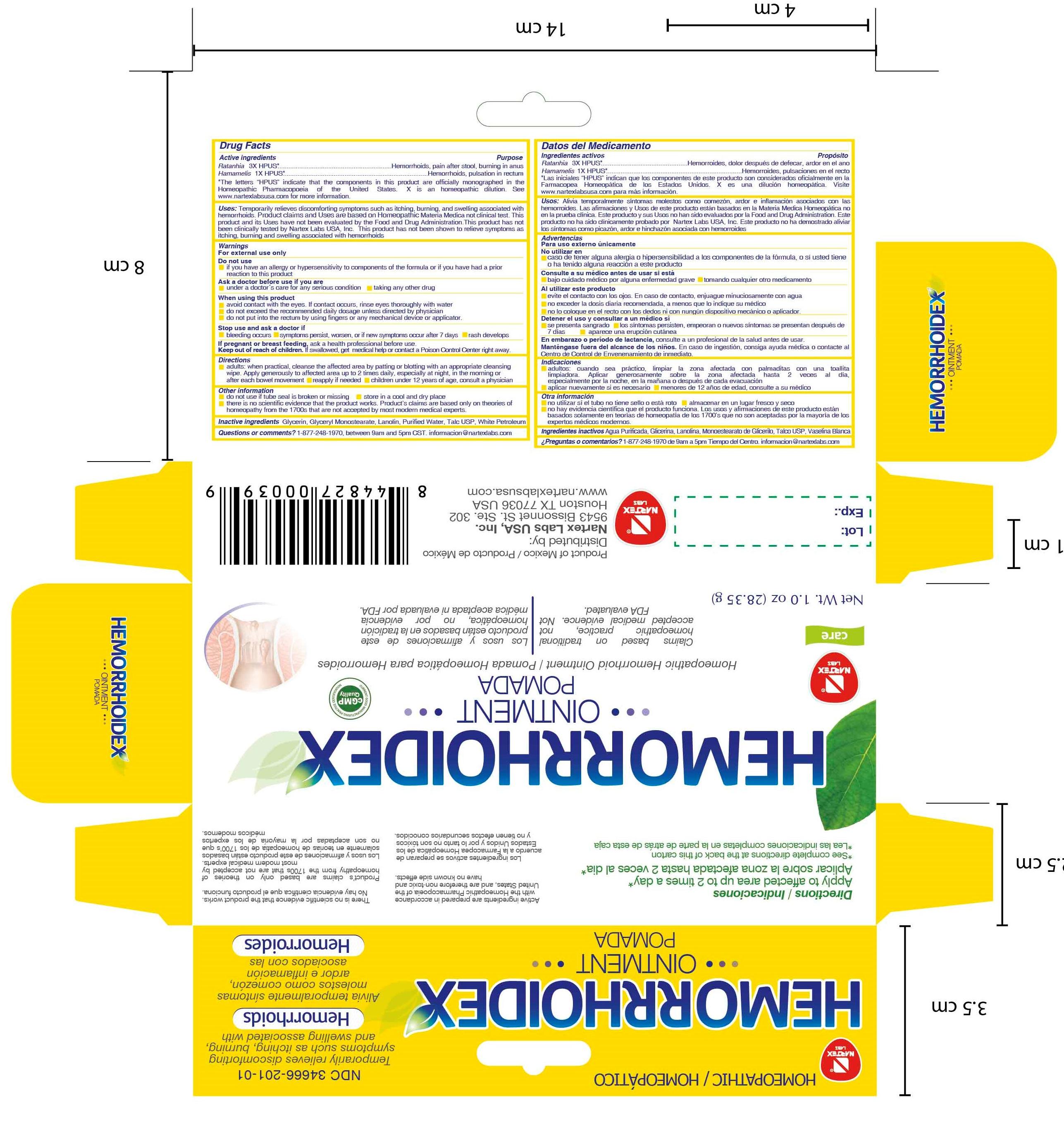 DRUG LABEL: Hemorrhoidex
NDC: 34666-201 | Form: OINTMENT
Manufacturer: Nartex Laboratorios Homeopaticos SA DE CV
Category: homeopathic | Type: HUMAN OTC DRUG LABEL
Date: 20220228

ACTIVE INGREDIENTS: KRAMERIA LAPPACEA ROOT 3 [hp_X]/28.35 g; HAMAMELIS VIRGINIANA ROOT BARK/STEM BARK 1 [hp_X]/28.35 g
INACTIVE INGREDIENTS: GLYCERIN; LANOLIN; GLYCERYL MONOSTEARATE; TALC; WATER; WHITE PETROLATUM

Drug Facts

Active Ingredients

Ratanhia........................3X HPUS

Hamamelis....................1X HPUS

Purpose

Ratanhia........................3X HPUS........Hemorrhoids, pain after stool, burning in anus
Hamamelis....................1X HPUS.........Hemorrhoids, pulsation in rectum
The letters "HPUS" indicate that the components in this product are officially monographed in the Homeopathic Pharmacopoeia of the United States. TINC is a homeopathic dilution: see www.nartexlabusa.com for details.

Uses

Temporarily relieves discomforting symptoms such as itching, burning, and swelling associated with hemorrhoids. Product Uses are based on Homeopathic Materia Medica.
This product and its Uses have not been evaluated by the Food and Drug Administration. This product has not been clinically tested by Nartex Labs USA, Inc.

Warnings

For external use only

Do not use

- if you have an allergy or hypersensitivity to components of the formula or if you have had a prior reaction to this product

Ask a doctor before use if you are

- under a doctor's care for any serious condition
- taking any other drug

When using this product

- avoid contact with the eyes. If contact occurs, rinse eyes thoroughly with water
- do not exceed the recommended daily dosage unless directed by physician

Stop use and ask a doctor if

- bleeding occurs
- symptoms persist, worse, or if new symptoms occur after 7 days
- rash develops

PREGNANCY OR BREAST FEEDING

If pregnant or breast feeding, ask a health professional before use.

Keep out of reach of children. If swallowed, get medical help or contact a Poison Control Center right away.

Directions

- adults: when practical, cleanse the affected area by patting or blotting with an appropriate cleansing wipe. Apply generously to affected area up to 2 times daily, especially at night, in the morning or after each bowel movement
- reapply if needed
- children under 12 years of age, consult a physician

Other Information

- do not use if plastic seal around cap is broken or missing
- store in a cool and dry place

Inactive Ingredients

Glycerin, Glyceryl Monostearate, Lanolin, Purified Water, Talc USP, White petrolatum

Questions or comments?

1-877-248-1970, between 9am and 5pm PT.
informacion@nartexlabs.com

DESCRIPTION

Distributed by:

Nartex Labs USA, Inc.
11711 Memorial dr #685
Houston TX 77024
www.nartexlabusa.com

Principal Display Panel

HEMORRHOIDEX

ointment

Homeopathic Hemorrhoid Ointment
Net Wt. 1.0 oz (28.35g)